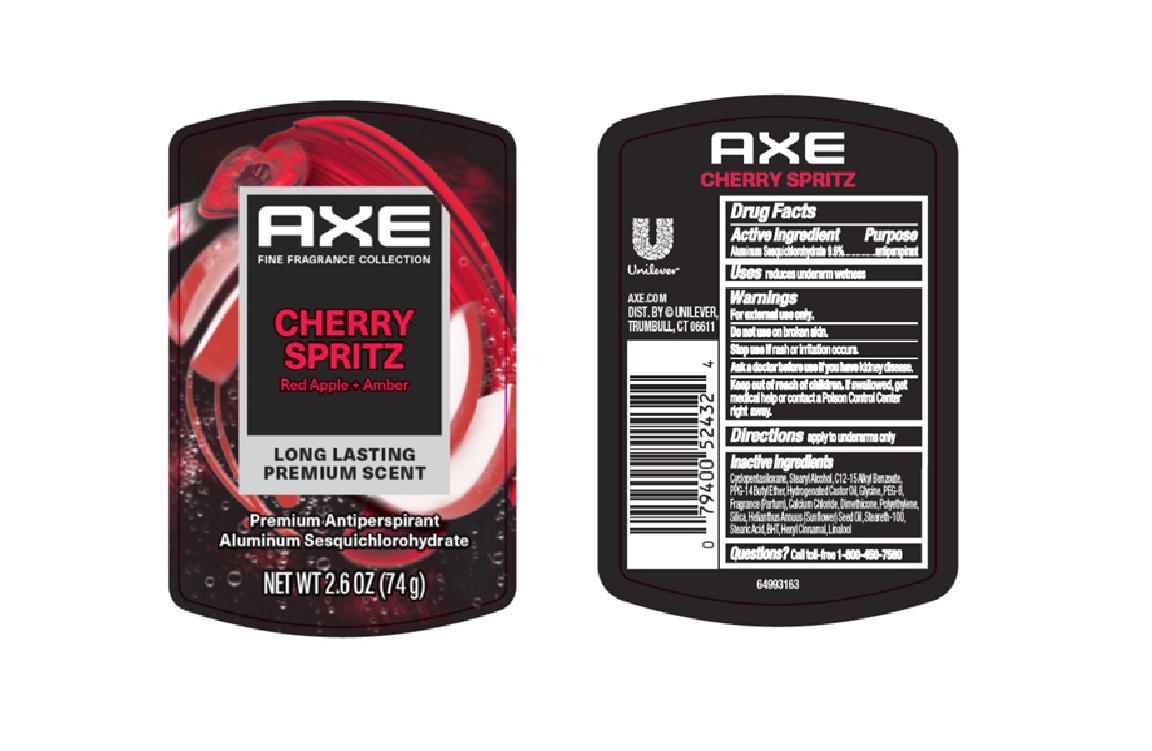 DRUG LABEL: Axe
NDC: 64942-2380 | Form: STICK
Manufacturer: Conopco d/b/a Unilever
Category: otc | Type: HUMAN OTC DRUG LABEL
Date: 20250718

ACTIVE INGREDIENTS: ALUMINUM SESQUICHLOROHYDRATE 9.6 g/100 g
INACTIVE INGREDIENTS: POLYETHYLENE; STEARIC ACID; C12-15 ALKYL BENZOATE; GLYCINE; PEG-8; HEXYL CINNAMAL; LINALOOL; CALCIUM CHLORIDE; STEARETH-100; STEARYL ALCOHOL; PPG-14 BUTYL ETHER; HYDROGENATED CASTOR OIL; DIMETHICONE; CYCLOPENTASILOXANE; SILICA; BHT; HELIANTHUS ANNUUS (SUNFLOWER) SEED OIL

Axe Cherry Spritz Red Apple and Amber Long Lasting Premium Scent Premium Antiperspirant

DESCRIPTION

Axe Cherry Spritz Red Apple and Amber Long Lasting Premium Scent Premium Antiperspirant

ACTIVE INGREDIENT

Aluminum Sesquichlorohydrate 9.6%

PURPOSE

Antiperspirant

INDICATIONS AND USAGE

apply to underarms only

WARNINGS

For external use only.
• Do not use on broken skin.• Ask a doctor before
use if you have kidney disease. • Stop use if rash or irritation occurs.

Keep out of reach of children. If swallowed,get medical help or contact a Poison Control Center right away

DOSAGE AND ADMINISTRATION

apply to underarms only

INACTIVE INGREDIENT

Cyclopentasiloxane,Stearyl Alcohol,C12-15 Alkyl Benzoate, PPG-14 Butyl Ether,Hydrogenated Castor Oil,Glycine,PEG-8, Fragrance (Parfum),Calcium Chloride,Dimethicone,Polyethylene, Silica,Helianthus Annuus (Sunflower) Seed Oil,Steareth-100, Stearic Acid,BHT,Hexyl Cinnamal,Linalool

QUESTIONS

call 1-800-761-3683